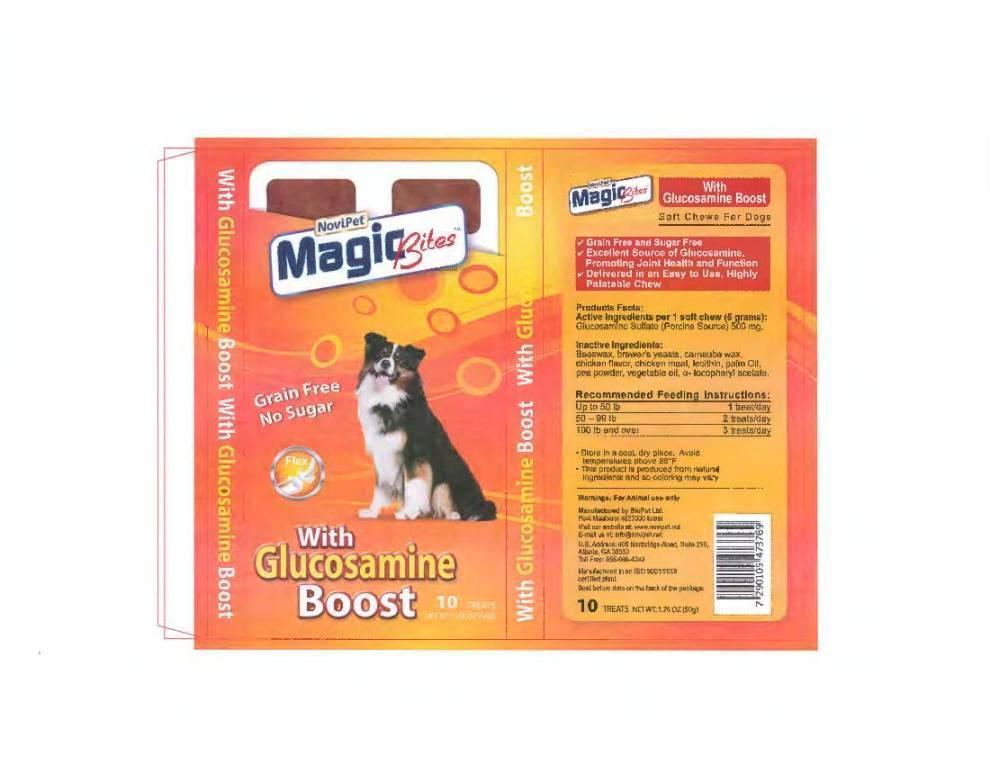 DRUG LABEL: Novipet
NDC: 45732-075 | Form: TABLET, CHEWABLE
Manufacturer: Novipet, Inc.
Category: animal | Type: OTC ANIMAL DRUG LABEL
Date: 20140122

ACTIVE INGREDIENTS: GLUCOSAMINE SULFATE 500 mg/1 1

Novipet Magic Bites for Dogs

FRONT PANEL

NoviPet Magic Bites

Grain Free

No Sugar

with Glucosamine Boost

10 Treats

NET WT. 1.76 OZ (50g)

Back Panel

Magic Bites with Glucosamine Boost

Soft Chews for Dogs

Grain Free and Sugar Free

Excellent Source of Glucosamine,

Promoting Joint Health and Function

Delivered in an Easy to Use, Highly

Palatable Chew

ACTIVE INGREDIENT

Product Facts:

Active Ingredients per 1 soft chew (5 grams)
Glucosamine sulfate (Porcine Source) 500 mg

Inactive Ingredients:

Beeswax, brewer's yeasts, carnauba wax,

chicken flavor, chicken meal, lecithin, palm Oil,

pea powder, vegetable oil, a- tocopheryl acetate.

DOSAGE AND ADMINISTRATION

Recommended Feeding Instructions:

Up to 50 lb | 1 treat/day
50 - 99 lb | 2 treats/day
100 lb and over | 3 treats/day

STORAGE AND HANDLING

Store in a cool, dry place.
Avoid temperatures above 86^0F.
This product is produced from natural
ingredients and so coloring may vary.

Warnings: For Animal use only

Manufactured by BioPet Ltd.

Post Maabarot 4023000 Israel

Visit our website at: www.novipet.net

E-mail us at: info@novipetnet

U.S. Address: 400 Northridge Road, Suite 250,

Atlanta, GA 30350

Toll Free: 855-668-4243

Manufactured in an ISO 9001:2008

certified plant

Best before date on the back of the package

10 TREATS NET WT. 1.76 OZ (50g)

Magic Bites label image